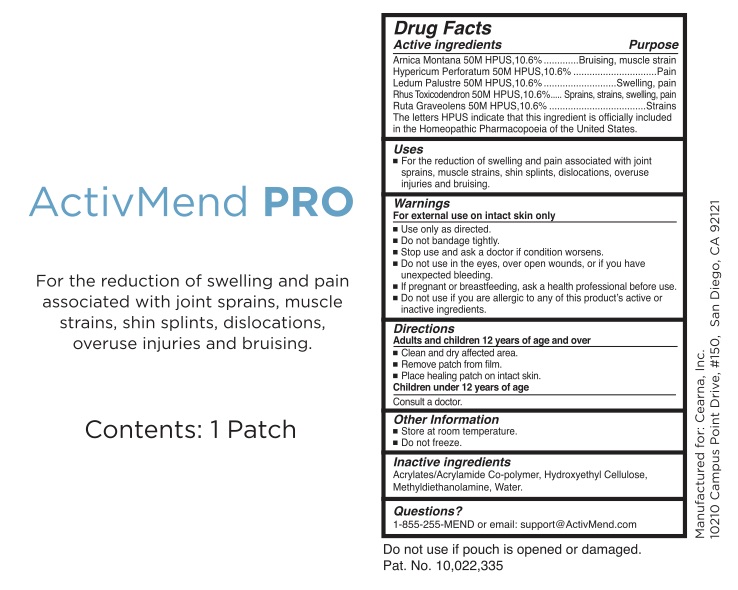 DRUG LABEL: ActivMend Pro
NDC: 76277-123 | Form: PATCH
Manufacturer: Cearna, Inc.
Category: homeopathic | Type: HUMAN OTC DRUG LABEL
Date: 20230110

ACTIVE INGREDIENTS: HYPERICUM PERFORATUM 50 [hp_M]/1 g; LEDUM PALUSTRE TWIG 50 [hp_M]/1 g; ARNICA MONTANA 50 [hp_M]/1 g; TOXICODENDRON PUBESCENS LEAF 50 [hp_M]/1 g; RUTA GRAVEOLENS FLOWERING TOP 50 [hp_M]/1 g
INACTIVE INGREDIENTS: BUTYL ACRYLATE/METHYL METHACRYLATE/METHACRYLIC ACID COPOLYMER (18000 MW); METHYL DIETHANOLAMINE; WATER; HYDROXYETHYL CELLULOSE, UNSPECIFIED

ActivMend Pro

Active Ingredients for Healing Gels:

Arnica Montana 50M

Hypericum Perforatum 50M

Ledum Palustre 50M

Rhus toxicodendron 50M

Ruta graveolens 50M

Purpose

Arnica Montana 50M...........................Bruising, muscle strain

Hypericum Perforatum 50M................Pain

Ledum Palustre 50M...........................Swelling, pain

Rhus toxicodendron 50M....................Sprains, strains, swelling, pain

Ruta graveolens 50M..........................Strains

Uses

For the reduction of swelling and pain associated with joint sprains, muscle strains, shin splints, dislocations, overuse injuries, and bruising.

Warnings

For external use on intact skin only

- Use only as directed.
- Do not bandage tightly.
- Stop use and ask a doctor if condition worsens.
- Do not use in the eyes, over open wounds, or if you have unexpected bleeding.
- If pregnant or breast-feeding, ask a health professional before use.
- Do not use if you are allergic to any of this product's active or ingredients.

Do not use:

Do not use in the eyes, over open wounds, or if you have unexpected bleeding

Stop use and ask a doctor if condition worsens

PREGNANCY OR BREAST FEEDING

I f pregnant or breast-feeding ask a health professional before use.

Keep out of reach of children.

Directions

Adults and Children 12 years of age and over

- Clean and dry affected area.
- Remove patch from film.
- Place healing pads on intact skin.
- Wear one activMend patch up to 24 hours.

Children under 12 years of age - Consult a doctor

Other information

Store at room temperature.

Do not freeze.
Tightly reseal pouch containing unused patches.

Inactive Ingredients

Acrylates/Acrylamide Co-polymer, Hydroxyethyl Cellulose, Methyldiethanolamine, Water

Questions?

1-855-255-MEND (6363)

or email: Support@ActivMend.com

The letters HPUS indicate that the component(s) in this product is (are) officially monographed in the Homeopathic Pharmacopeia of the United States.

Do not use if pouches are open or damaged.